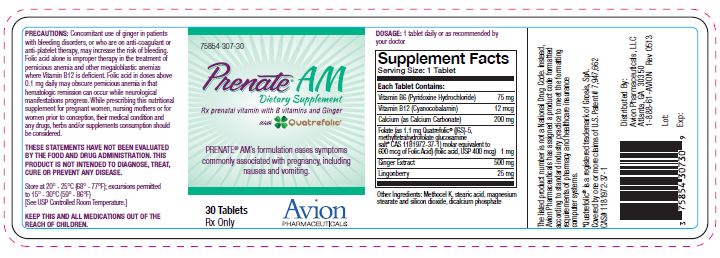 DRUG LABEL: Prenate AM
NDC: 75854-307 | Form: TABLET, COATED
Manufacturer: Avion Pharmaceuticals, LLC
Category: prescription | Type: HUMAN PRESCRIPTION DRUG LABEL
Date: 20180105

ACTIVE INGREDIENTS: PYRIDOXINE HYDROCHLORIDE 75 mg/1 1; CYANOCOBALAMIN 12 ug/1 1; CALCIUM CARBONATE 200 mg/1 1; FOLIC ACID 1 mg/1 1
INACTIVE INGREDIENTS: GINGER 500 mg/1 1; LINGONBERRY 25 mg/1 1; HYPROMELLOSES; STEARIC ACID; MAGNESIUM STEARATE; SILICON DIOXIDE; CALCIUM PHOSPHATE, DIBASIC, ANHYDROUS

PRENATE AM®

Dietary Supplement
Rx prenatal vitamin with B vitamins and Ginger
With
Quatrefolic®

Rx Only

DESCRIPTION

DESCRIPTION: PRENATE® AM is a yellow, oval, oil- and water-soluble, multivitamin/multimineral, film-coated tablet debossed with "Prenate" on one side and "AM" on the other.

Supplement Facts Serving Size: 1 Tablet
Each Tablet Contains:
Vitamin B6 (Pyridoxine Hydrochloride) | 75 mg
Vitamin B12 (Cyanocobalamin) | 12 mcg
Calcium (as Calcium Carbonate) | 200 mg
Folate (as 1.1 mg Quatrefolic® ((6S)-5,methyltetrahydrofolate glucosamine salt* CAS 1181972-37-1) molar equivalent to 600 mcg of Folic Acid) (folic acid, USP 400 mcg) | 1 mg
Ginger Extract | 500 mg
Lingonberry | 25 mg

INACTIVE INGREDIENT

OTHER INGREDIENTS: Methocel K, stearic acid, magnesium stearate and silicon dioxide, dicalcium phosphate

BOXED WARNING

PRECAUTIONS: Concomitant use of ginger in patients with bleeding disorders, or who are on anti-coagulant or anti-platelet therapy, may increase the risk of bleeding. Folic acid alone is improper therapy in the treatment of pernicious anemia and other megaloblastic anemias where Vitamin B12 is deficient. Folic acid in doses above 0.1 mg daily may obscure pernicious anemia in that hematologic remission can occur while neurological manifestations progress. While prescribing this nutritional supplement for pregnant women, nursing mothers or for women prior to conception, their medical condition and any drugs, herbs and/or supplements consumption should be considered.

DOSAGE AND ADMINISTRATION: One tablet daily or as directed by your doctor.

THESE STATEMENTS HAVE NOT BEEN EVALUATED BY THE FOOD AND DRUG ADMINISTRATION. THIS PRODUCT IS NOT INTENDED TO DIAGNOSE, TREAT, CURE OR PREVENT ANY DISEASE.

STORAGE AND HANDLING

Store at 20° - 25°C (68° - 77°F); excursions permitted to 15° - 30°C (59° - 86°F) [See USP Controlled Room Temperature.]

WARNINGS

KEEP THIS AND ALL MEDICATIONS OUT OF THE REACH OF CHILDREN.

DISTRIBUTED BY:
Avion Pharmaceuticals, LLC
Atlanta, GA 30350 1-888-61-AVION Rev. 0513

The listed product number is not a National Drug Code. Instead, Avion Pharmaceuticals has assigned a product code formatted according to standard industry practice to meet the formatting requirements of pharmacy and healthcare insurance computer systems.

*Quatrefolic® is a registered trademark of Gnosis, SpA. Covered by one or more claims of U.S. Patent # 7,947,662 CAS# 1181972-37-1

PRENATE® AM is a registered trademark of Acella Pharmaceuticals, LLC. Under license from Acella Pharmaceuticals, LLC. All rights reserved.

PACKAGE LABEL.PRINCIPAL DISPLAY PANEL

75854-307-30

Prenate® Am
Dietary Supplement
Rx prenatal vitamin with B vitamins and Ginger
With
Quatrefolic®

PRENATE® AM’s formulation eases symptoms
commonly associated with pregnancy, including
nausea and vomiting.

30 Tablets
Rx Only

Avion
PHARMACEUTICALS